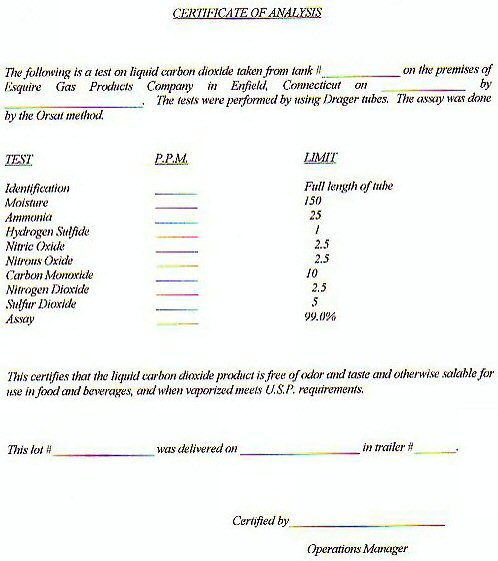 DRUG LABEL: CARBON DIOXIDE
NDC: 53620-101 | Form: GAS
Manufacturer: Esquire Gas Products Company, Inc
Category: prescription | Type: HUMAN PRESCRIPTION DRUG LABEL
Date: 20100101

ACTIVE INGREDIENTS: CARBON DIOXIDE 99 L/100 L

CARBON DIOXIDE CERTIFICATE OF ANALYSIS

CERTIFICATE OF ANALYSIS

THE FOLLOWING IS A TEST ON LIQUID CARBON DIOXIDE TAKEN FROM TANK # _____________ ON THE PREMISES OF ESQUIRE GAS PRODUCTS COMPANY IN ENFIELD, CONNECTICUT ON _________ BY _____________. THE TESTS WERE PERFORMED BY USING DRAGER TUBES. THE ASSAY WAS DONE BY THE ORSAT METHOD.

TEST PPM LIMIT

IDENTIFICATION _________ FULL LENGTH OF TUBE

MOISTURE __________ 150

AMMONIA __________ 25

HYDROGEN SULFIDE ___________ 1

NITRIC OXIDE ___________ ` 2.5

NITROUS OXIDE ____________ 2.5

CARBON MONOXIDE ___________ 10

NITROGEN DIOXIDE ____________ 2.5

SULFUR DIOXIDE ____________ 5

ASSAY _____________ 99.0%

THIS CERTIFIES THAT THE LIQUID CARBON DIOXIDE PRODUCT IS FREE OF ODOR AND TASTE AND OTHERWISE SALABLE FOR USE IN FOOD AND BEVERAGES, AND WHEN VAPORIZED MEETS U.S.P. REQUIREMENTS

THIS LOT #________________ WAS DELIVERED ON _____________ IN TRAILER #___________________

CERTIFIED BY ______________________ OPERATIONS MANAGER